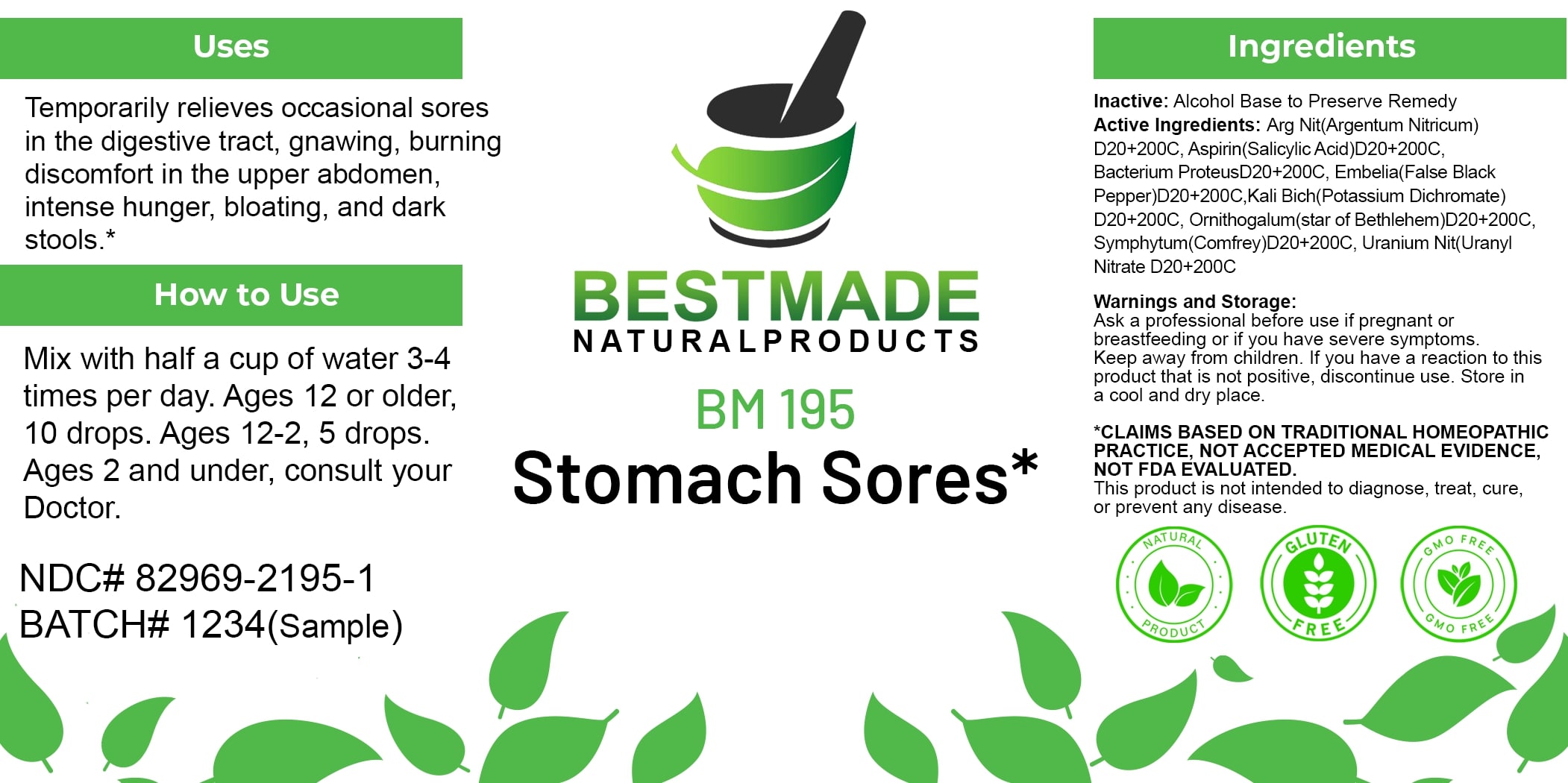 DRUG LABEL: Bestmade Natural Products BM195
NDC: 82969-2195 | Form: LIQUID
Manufacturer: Bestmade Natural Products
Category: homeopathic | Type: HUMAN OTC DRUG LABEL
Date: 20250225

ACTIVE INGREDIENTS: EMBELIA RIBES WHOLE 200 [hp_C]/200 [hp_C]; POTASSIUM DICHROMATE 200 [hp_C]/200 [hp_C]; URANYL NITRATE HEXAHYDRATE 200 [hp_C]/200 [hp_C]; ASPIRIN 200 [hp_C]/200 [hp_C]; ORNITHOGALUM UMBELLATUM 200 [hp_C]/200 [hp_C]; PROTEUS VULGARIS 200 [hp_C]/200 [hp_C]; COMFREY ROOT 200 [hp_C]/200 [hp_C]; SILVER NITRATE 200 [hp_C]/200 [hp_C]
INACTIVE INGREDIENTS: ALCOHOL 200 [hp_C]/200 [hp_C]

BM195

DOSAGE AND ADMINISTRATION

How to Use

Mix with half a cup of water 3-4 times per day. Ages 12 or older, 10 drops. Ages 12-2, 5 drops. Ages 2 and under, consult your Doctor.

Uses

Temporarily relieves occasional sores in the digestive tract, gnawing, burning discomfort in the upper abdomen, intense hunger, bloating, and dark stools.*

*CLAIMS BASED ON TRADITIONAL HOMEOPATHIC PRACTICE, NOT ACCEPTED MEDICAL EVIDENCE, NOT FDA EVALUATED.

This product is not intended to diagnose, treat, cure, or prevent any disease.

Uses

Temporarily relieves occasional sores in the digestive tract, gnawing, burning discomfort in the upper abdomen, intense hunger, bloating, and dark stools.*

*CLAIMS BASED ON TRADITIONAL HOMEOPATHIC PRACTICE, NOT ACCEPTED MEDICAL EVIDENCE, NOT FDA EVALUATED.

This product is not intended to diagnose, treat, cure, or prevent any disease.

INACTIVE INGREDIENT

Ingredients

Inactive: Alcohol Base to Preserve Remedy

ACTIVE INGREDIENT

Active Ingredients: Arg Nit(Argentum Nitricum) D20+200C, Aspirin(Salicylic Acid)D20+200C, Bacterium ProteusD20+200C, Embelia(False Black Pepper)D20+200C, Kali Bich(Potassium Dichromate) D20+200C, Ornithogalum(Star of Bethlehem)D20+200C, Symphytum(Comfrey)D20+200C, Uranium Nit(Uranyl Nitrate)D20+200C

KEEP OUT OF REACH OF CHILDREN

Warnings and Storage:

Ask a professional before use if pregnant or breastfeeding or if you have severe symptoms. Keep away from children. If you have a reaction to this product that is not positive, discontinue use. Store in a cool and dry place.

Warnings and Storage:

Ask a professional before use if pregnant or breastfeeding or if you have severe symptoms. Keep away from children. If you have a reaction to this product that is not positive, discontinue use. Store in a cool and dry place.

*CLAIMS BASED ON TRADITIONAL HOMEOPATHIC PRACTICE, NOT ACCEPTED MEDICAL EVIDENCE, NOT FDA EVALUATED.

This product is not intended to diagnose, treat, cure, or prevent any disease.

Entire package label